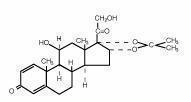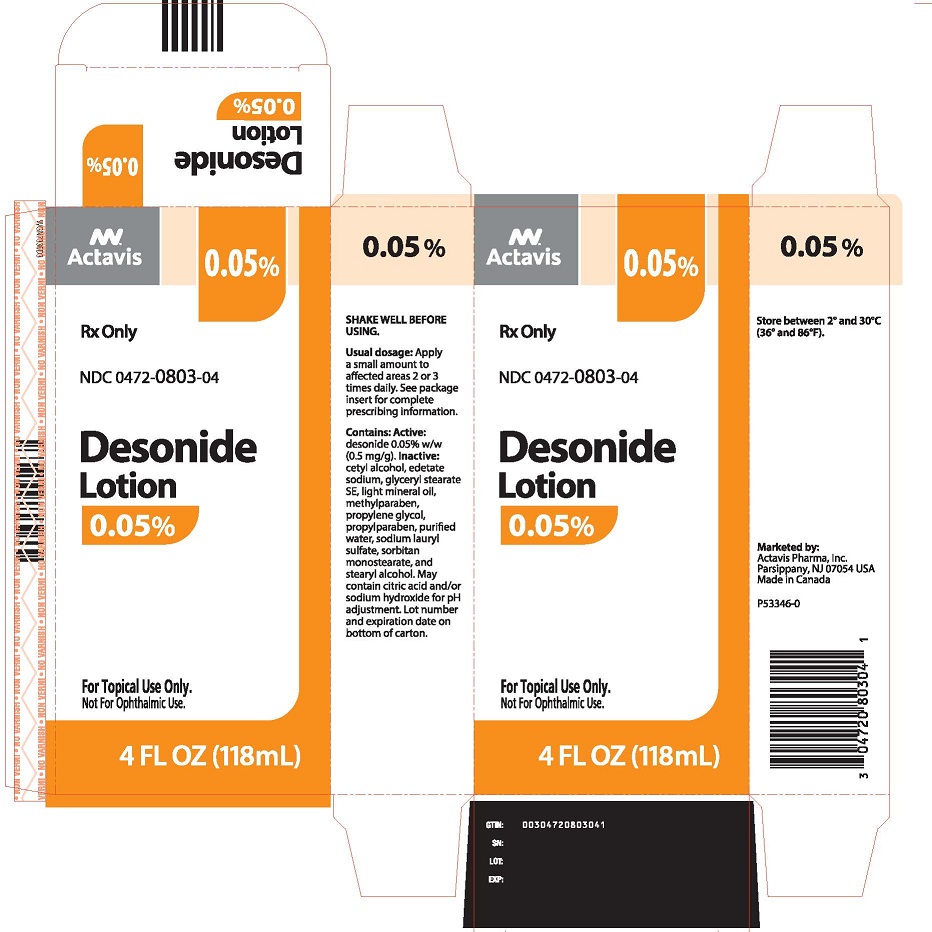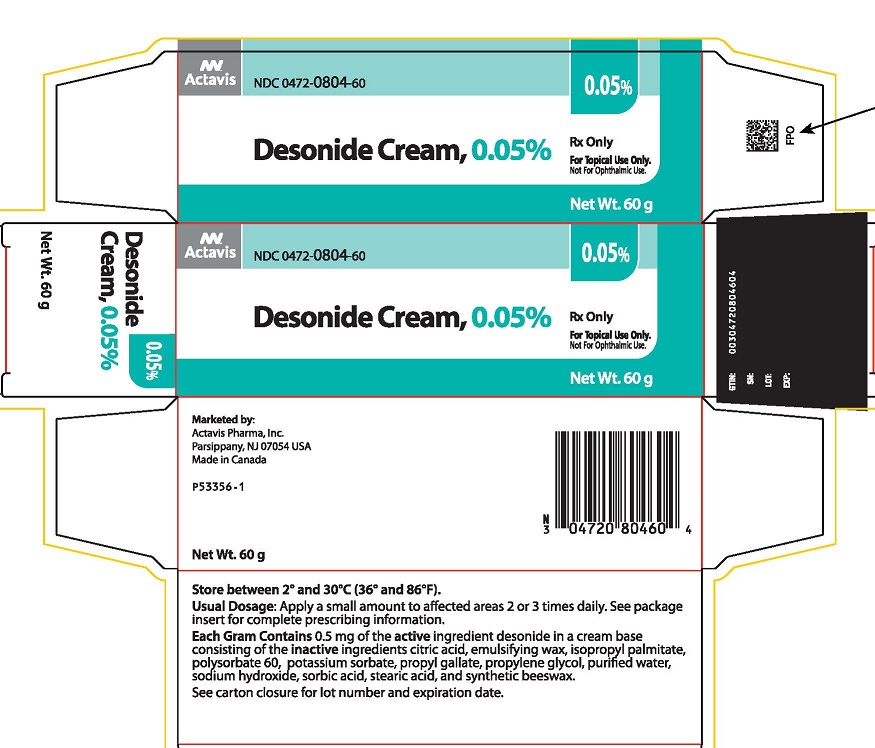 DRUG LABEL: Desonide
NDC: 0472-0804 | Form: CREAM
Manufacturer: Actavis Pharma, Inc.
Category: prescription | Type: HUMAN PRESCRIPTION DRUG LABEL
Date: 20250908

ACTIVE INGREDIENTS: DESONIDE 0.5 mg/1 g
INACTIVE INGREDIENTS: ANHYDROUS CITRIC ACID; ISOPROPYL PALMITATE; POLYSORBATE 60; POTASSIUM SORBATE; PROPYL GALLATE; PROPYLENE GLYCOL; WATER; SODIUM HYDROXIDE; SORBIC ACID; STEARIC ACID

DESONIDE Rx Only
cream 0.05%
and lotion 0.05%
For Dermatologic Use Only –
Not for Ophthalmic Use –

DESCRIPTION:

Desonide Cream 0.05% and Lotion 0.05% contain desonide (Pregna-1,4-diene-3,20-dione,11,21-dihydroxy-16,17 [(1-methylethylidene)bis(oxy)]-,(11β,16α)- a synthetic nonfluorinated corticosteroid for topical dermatologic use. The corticosteroids constitute a class of primarily synthetic steroids used topically as anti-inflammatory and anti-pruritic agents.

Chemically, desonide is C24H32O6. It has the following structural formula:

Desonide has the molecular weight of 416.51. It is a white to off white odorless powder which is soluble in methanol and practically insoluble in water.

Each gram of Desonide Cream contains 0.5 mg of desonide in a base of citric acid, emulsifying wax, isopropyl palmitate, polysorbate 60, potassium sorbate, propyl gallate, propylene glycol, purified water, sodium hydroxide, sorbic acid, stearic acid, and synthetic beeswax.

Each gram of Desonide Lotion contains 0.5 mg of desonide in a base of cetyl alcohol, edetate sodium, glyceryl stearate SE, light mineral oil, methylparaben, propylene glycol, propylparaben, purified water, sodium lauryl sulfate, sorbitan monostearate, and stearyl alcohol. May contain citric acid and/or sodium hydroxide for pH adjustment.

CLINICAL PHARMACOLOGY:

Like other topical corticosteroids, desonide has anti-inflammatory, antipruritic and vasoconstrictive properties. The mechanism of the anti-inflammatory activity of the topical steroids, in general, is unclear. However, corticosteroids are thought to act by the induction of phospholipase A2 inhibitory proteins, collectively called lipocortins. It is postulated that these proteins control the biosynthesis of potent mediators of inflammation such as prostaglandins and leukotrienes by inhibiting the release of their common precursor arachidonic acid. Arachidonic acid is released from membrane phospholipids by phospholipase A2.

Pharmacokinetics:

The extent of percutaneous absorption of topical corticosteroids is determined by many factors including the vehicle and the integrity of the epidermal barrier. Occlusive dressings with hydrocortisone for up to 24 hours have not been demonstrated to increase penetration; however, occlusion of hydrocortisone for 96 hours markedly enhances penetration. Topical corticosteroids can be absorbed from normal intact skin. Inflammation and/or other disease processes in the skin may increase percutaneous absorption.

Studies performed with Desonide Cream and Lotion indicate that they are in the low to medium range of potency as compared with other topical corticosteroids.

INDICATIONS AND USAGE:

Desonide Cream and Lotion are low to medium potency corticosteroids indicated for the relief of the inflammatory and pruritic manifestations of corticosteroid responsive dermatoses.

CONTRAINDICATIONS:

Desonide Cream and Lotion are contraindicated in those patients with a history of hypersensitivity to any of the components of the preparations.

PRECAUTIONS:

General:

Systemic absorption of topical corticosteroids can produce reversible hypothalamic-pituitary-adrenal (HPA) axis suppression with the potential for glucocorticosteroid insufficiency after withdrawal of treatment. Manifestations of Cushing’s syndrome, hyperglycemia, and glucosuria can also be produced in some patients by systemic absorption of topical corticosteroids while on treatment.

Patients applying a topical steroid to a large surface area or to areas under occlusion should be evaluated periodically for evidence of HPA axis suppression. This may be done by using the ACTH stimulation, A.M. plasma cortisol, and urinary free cortisol tests. Patients receiving superpotent corticosteroids should not be treated for more than 2 weeks at a time and only small areas should be treated at any one time due to the increased risk of HPA axis suppression.

If HPA axis suppression is noted, an attempt should be made to withdraw the drug, to reduce the frequency of application, or to substitute a less potent corticosteroid. Recovery of HPA axis function is generally prompt and complete upon discontinuation of topical corticosteroids. Infrequently, signs and symptoms of glucocorticosteroid insufficiency may occur requiring supplemental systemic corticosteroids. For information on systemic supplementation, see prescribing information for those products.

Pediatric patients may be more susceptible to systemic toxicity from equivalent doses due to their larger skin surface to body mass ratios. (See PRECAUTIONS - Pediatric use).

If irritation develops, Desonide Cream or Lotion should be discontinued and appropriate therapy instituted. Allergic contact dermatitis with corticosteroids is usually diagnosed by observing failure to heal rather than noting a clinical exacerbation as with most topical products not containing corticosteroids. Such an observation should be corroborated with appropriate diagnostic patch testing.

If concomitant skin infections are present or develop, an appropriate antifungal or antibacterial agent should be used. If a favorable response does not occur promptly, use of Desonide Cream or Lotion should be discontinued until the infection has been adequately controlled.

Information for patients:

Patients using topical corticosteroids should receive the following information and instructions:

1. This medication is to be used as directed by the physician. It is for external use only. Avoid contact with the eyes.
2. This medication should not be used for any disorder other than that for which it was prescribed.
3. The treated skin area should not be bandaged or otherwise covered or wrapped so as to be occlusive unless directed by the physician.
4. Patients should report to their physician any signs of local adverse reactions.

Laboratory tests:

The following tests may be helpful in evaluating patients for HPA axis suppression:

ACTH stimulation test

A.M. plasma cortisol test

Urinary free cortisol test

Carcinogenesis, mutagenesis, impairment of fertility:

Long-term animal studies have not been performed to evaluate the carcinogenic potential or the effect on reproduction with the use of Desonide Cream and Lotion.

Pregnancy:

Teratogenic Effects: Pregnancy category C:

Corticosteroids have been shown to be teratogenic in laboratory animals when administered systemically at relatively low dosage levels. Some corticosteroids have been shown to be teratogenic after dermal application in laboratory animals. Animal reproduction studies have not been conducted with Desonide Cream or Lotion. It is also not known whether Desonide Cream or Lotion can cause fetal harm when administered to a pregnant woman or can affect reproduction capacity. Desonide Cream and Lotion should be given to a pregnant woman only if clearly needed.

Nursing mothers:

Systemically administered corticosteroids appear in human milk and could suppress growth, interfere with endogenous corticosteroid production, or cause other untoward effects. It is not known whether topical administration of corticosteroids could result in sufficient systemic absorption to produce detectable quantities in human milk. Because many drugs are excreted in human milk, caution should be exercised when Desonide Cream or Lotion is administered to a nursing woman.

Pediatric use:

Safety and effectiveness in pediatric patients have not been established. Because of a higher ratio of skin surface area to body mass, pediatric patients are at a greater risk than adults of HPA axis suppression when they are treated with topical corticosteroids. They are therefore also at greater risk of glucocorticosteroid insufficiency after withdrawal of treatment and of Cushing’s syndrome while on treatment. Adverse effects including striae have been reported with inappropriate use of topical corticosteroids in infants and children.

HPA axis suppression, Cushing’s syndrome, linear growth retardation, delayed weight gain and intracranial hypertension have been reported in children receiving topical corticosteroids. Manifestations of adrenal suppression in children include low plasma cortisol levels, and absence of response to ACTH stimulation. Manifestations of intracranial hypertension include bulging fontanelles, headaches, and bilateral papilledema.

ADVERSE REACTIONS:

In controlled clinical trials, the total incidence of adverse reactions associated with the use of desonide was approximately 8%. These were: stinging and burning approximately 3%, irritation, contact dermatitis, condition worsened, peeling of skin, itching, intense transient erythema, and dryness/scaliness, each less than 2%.

The following additional local adverse reactions have been reported infrequently with other topical corticosteroids, and they may occur more frequently with the use of occlusive dressings, especially with higher potency corticosteroids. These reactions are listed in an approximate decreasing order of occurrence: folliculitis, acneiform eruptions, hypopigmentation, perioral dermatitis, secondary infection, skin atrophy, striae, and miliaria.

OVERDOSAGE:

Topically applied Desonide Cream and Lotion can be absorbed in sufficient amounts to produce systemic effects (See PRECAUTIONS).

DOSAGE AND ADMINISTRATION:

Desonide Cream or Lotion should be applied to the affected areas as a thin film two or three times daily depending on the severity of the condition. SHAKE LOTION WELL BEFORE USING.

As with other corticosteroids, therapy should be discontinued when control is achieved. If no improvement is seen within 2 weeks, reassessment of diagnosis may be necessary.

Desonide Cream and Lotion should not be used with occlusive dressings.

HOW SUPPLIED:

Desonide Cream 0.05% is supplied in a tube containing:

15 g NDC 0472-0804-15

60 g NDC 0472-0804-60

Desonide Lotion 0.05% is supplied in bottles containing:

2 fl oz NDC 0472-0803-02

4 fl oz NDC 0472-0803-04

Storage Conditions: Store between 2° and 30°C (36° and 86°F).

Marketed by:

Actavis Pharma, Inc.
Parsippany, NJ 07054 USA
Made in Canada
P53355-1 Rev. March 2018

PACKAGE LABEL - Desonide Cream

Actavis

NDC 0472-0804-60

Rx Only
For Topical Use Only.
Not for Ophthalmic Use.

Desonide

Cream 0.05% NET WT. 60 g

Marketed by:
Actavis Pharma, Inc.
Parsippany, NJ 07054 USA
Made in Canada
P53356-1

Store between 2° and 30°C (36° and 86°F).

Usual dosage: Apply a small amount to affected areas 2 or 3 times daily. See package insert for complete prescribing information.

Each gram contains 0.5 mg of the active ingredient desonide in a cream base consisting of the inactive ingredients citric acid, emulsifying wax, isopropyl palmitate, polysorbate 60, potassium sorbate, propyl gallate, propylene glycol, purified water, sodium hydroxide, sorbic acid, stearic acid and synthetic beeswax.

See carton closure for lot number and expiration date.

PACKAGE LABEL - Desonide Lotion

Rx Only NDC 0472-0803-04

Desonide

Lotion 0.05%

For Topical Use Only.
Not for Ophthalmic Use.

4 FL OZ

(118 mL)

SHAKE WELL BEFORE USING.

Usual dosage: Apply a small amount to affected areas 2 or 3 times daily. See package insert for complete prescribing information.

Contains: Active: desonide 0.05% w/w (0.5 mg/g). Inactive: cetyl alcohol, edetate sodium, glyceryl stearate SE, light mineral oil, methylparaben, propylene glycol, propylparaben, purified water, sodium lauryl sulfate, sorbitan monostearate, and stearyl alcohol. May contain citric acid and/or sodium hydroxide for pH adjustment. Lot number and expiration date on bottom of carton.

Store between 2° AND 30°C (36° AND 86°F).

Marketed by:
Actavis Pharma, Inc.
Parsippany, NJ 07054 USA
Made in Canada
P53346-0